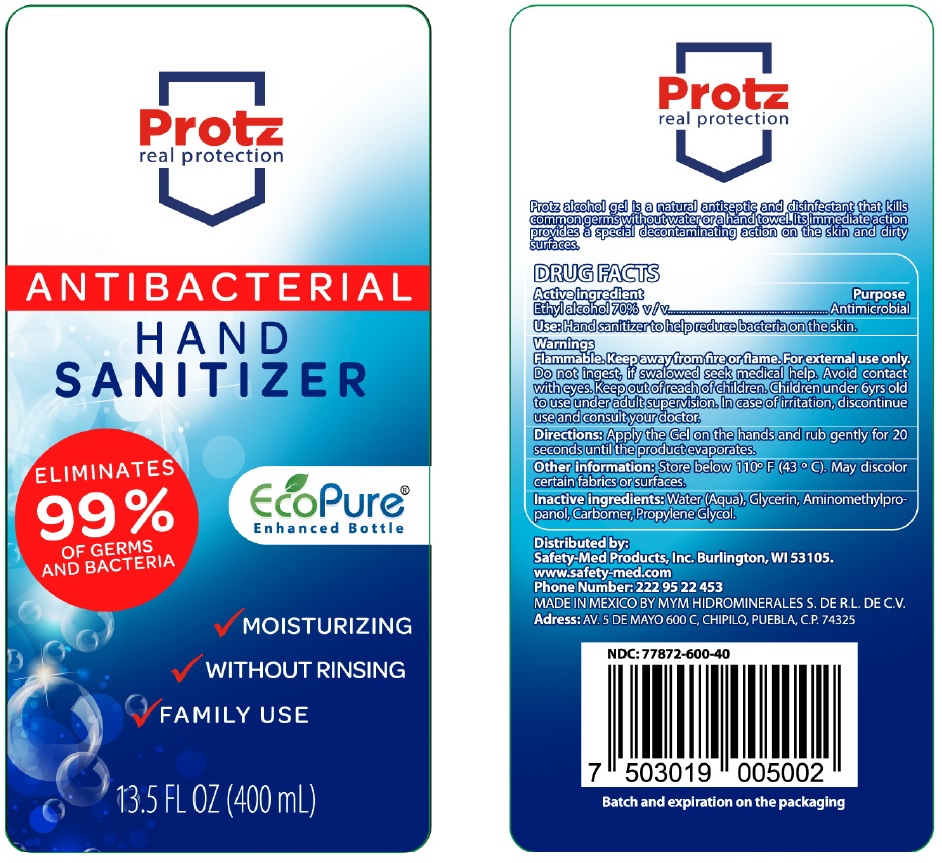 DRUG LABEL: Protz ANTIBACTERIAL HAND SANITIZER
NDC: 77872-600 | Form: GEL
Manufacturer: MYM Hidrominerales, S, de R.L. de C.V.
Category: otc | Type: HUMAN OTC DRUG LABEL
Date: 20200518

ACTIVE INGREDIENTS: ALCOHOL 70 mL/100 mL
INACTIVE INGREDIENTS: WATER; GLYCERIN; AMINOMETHYLPROPANOL; CARBOMER INTERPOLYMER TYPE A (ALLYL SUCROSE CROSSLINKED); PROPYLENE GLYCOL

Protz ANTIBACTERIAL HAND SANITIZER

Active ingredient

Ethyl alcohol 70% v/v

Purpose

Antimicrobial

INDICATIONS AND USAGE

Use: Hand sanitizer to help reduce bacteria on the skin.

Warnings

Flammable. Keep away from fire or flame. For external use only.

Do not ingest, if swallowed seek medical help. Avoid contact with eyes.

Keep out of reach of children. Children under 6yrs old to use under adult supervision. In case of irritation, discontinue use and consult your doctor.

DOSAGE AND ADMINISTRATION

Directions: Apply the Gel on the hands and rub gently for 20 seconds until the product evaporates.

Other information: Store below 110°F (43°C). May discolor certain fabrics or surfaces.

INACTIVE INGREDIENT

Inactive ingredients: Water (Aqua), Glycerin, Aminomethylpropanol, Carbomer, Propylene Glycol.

real protection

ELIMINATES 99% OF GERMS AND BACTERIA

EcoPure®

Enhanced Bottle

✓ MOISTURIZING

✓ WITHOUT RINSING

✓ FAMILY USE

Protz alcohol gel is a natural antiseptic and disinfectant that kills common germs without water or a hand towel. Its immediate action provides a special decontaminating action on the skin and dirty surfaces.

Distributed by:

Safety-Med Products, Inc. Burlington, WI 53105.

www.safety-med.com

Phone N umber: 222 95 22 453

MADE IN MEXICO BY MYM HIDROMINERALES S. DE R.L. DE C.V.

Address: AV. 5 DE MAYO 600 C, CHIPILO, PUEBLA, C.P. 74325

Batch and expiration on the packaging